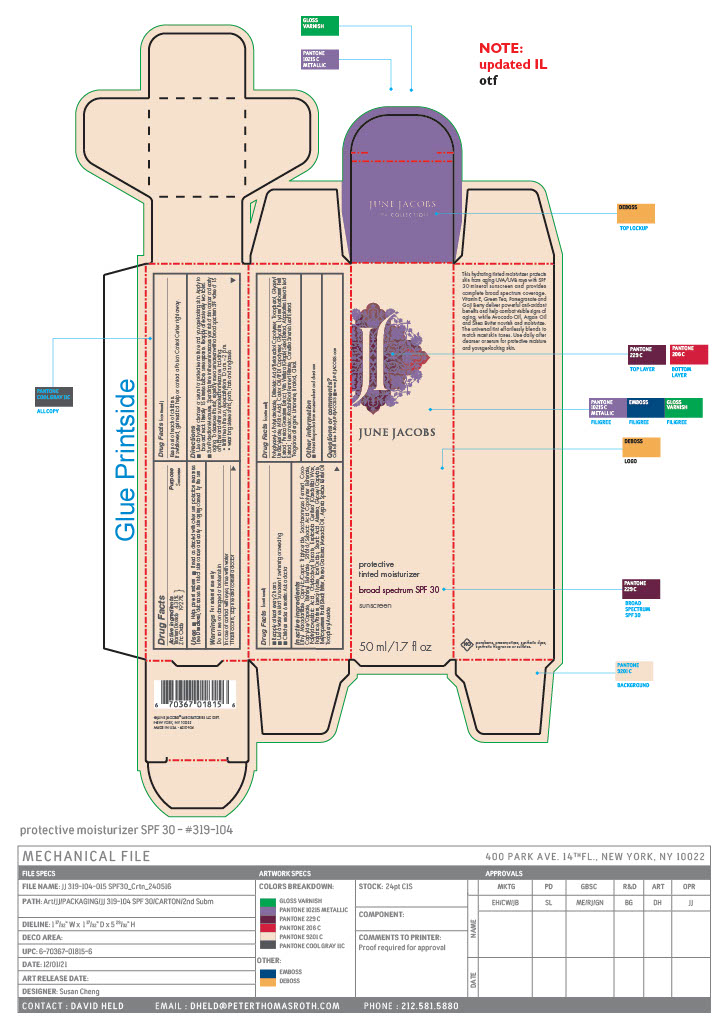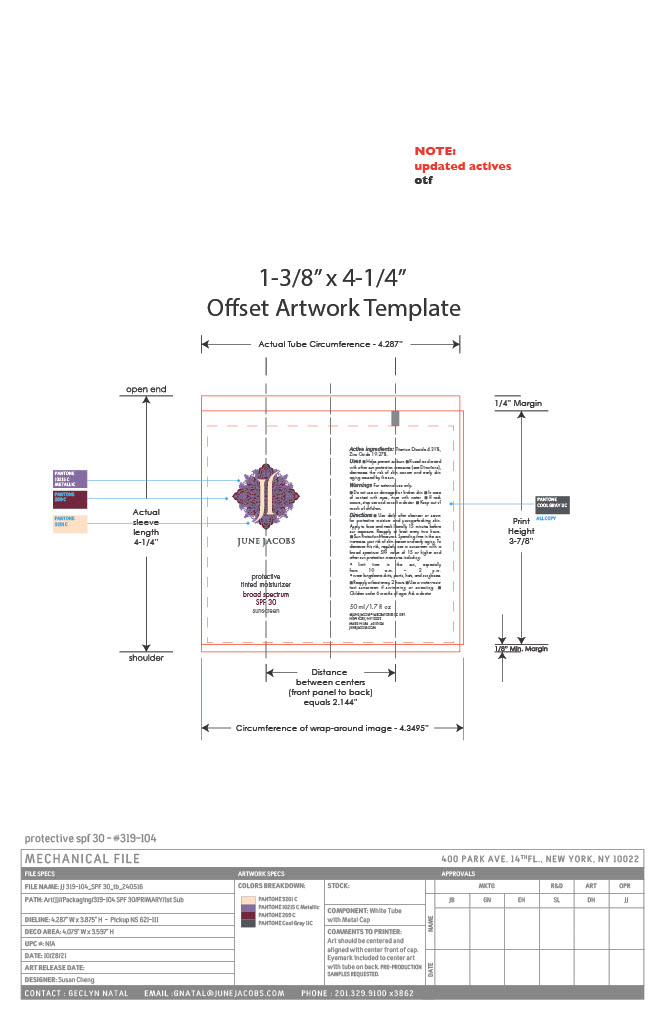 DRUG LABEL: Protective Tinted Moisturizer Broad Spectrum Sunscreen SPF 30
NDC: 65278-104 | Form: PASTE
Manufacturer: June Jacobs Labs LLC
Category: otc | Type: HUMAN OTC DRUG LABEL
Date: 20240520

ACTIVE INGREDIENTS: ZINC OXIDE 9.693 g/50.28 g; TITANIUM DIOXIDE 2.169 g/50.28 g
INACTIVE INGREDIENTS: GREEN TEA LEAF; LIMONENE, (+)-; LINALOOL, (+/-)-; SACCHAROMYCES CEREVISIAE; COCO-CAPRYLATE/CAPRATE; SUNFLOWER OIL; ARGAN OIL; MALIC ACID; GLYCERIN; PUNICA GRANATUM ROOT BARK; LAUROYL LYSINE; JUNIPER BERRY OIL; ASPALATHUS LINEARIS LEAF; LEUCONOSTOC/RADISH ROOT FERMENT FILTRATE; SHEA BUTTER; ETHYL MACADAMIATE; LITSEA OIL; GINGER OIL; TOCOPHEROL; GLYCERYL 1-UNDECYLENATE; CASTOR OIL; LYCIUM BARBARUM FRUIT; GLYCERYL CAPRYLATE; MEDIUM-CHAIN TRIGLYCERIDES; ALUMINUM OXIDE; AVOCADO OIL; .ALPHA.-TOCOPHEROL ACETATE; POLYGLYCERYL-6 POLYRICINOLEATE; DILINOLEIC ACID/BUTANEDIOL COPOLYMER; LAVANDIN OIL; VETIVER OIL; FERRIC OXIDE RED; STEARIC ACID; CAPRYLOYL GLYCERIN/SEBACIC ACID COPOLYMER (2000 MPA.S); POLYHYDROXYSTEARIC ACID (2300 MW); OCTYLDODECYL ERUCATE; AMYRIS BALSAMIFERA OIL; GERANIUM OIL, ALGERIAN TYPE; POGOSTEMON CABLIN LEAF OIL; GALBANUM; CITRAL; BEHENYL BEHENATE; CANDELILLA WAX; ORANGE OIL; VITIS VINIFERA SEED

June Jacobs Protective Tinted Moisturizer Broad Spectrum Sunscreen SPF 30

Active Ingredients

Titanium Dioxide........... 4.31%

Zinc Oxide....................19.27%

PURPOSE

Sunscreen

USES

- Helps prevent sunburn
- If used as directed with other sun protection measures (see Directions), decreases the risk of skin cancer and early skin aging caused by the sun

Warnings

For external use only

Do not use on damaged or broken skin

WHEN USING

- In case of contact with eyes, rinse with water
- If rash occurs, stop use and consult a doctor

Keep out of reach of children

If swallowed, get medical help or contact a Poison Control Center right away.

Directions

- Use daily after cleanser or serum for protective moisture and younger-looking skin. Apply to face and neck liberally 15 minutes before sun exposure. Reapply at least every two hours
- Sun Protection Measures. Spending time in the sun increases your risk of skin cancer and early aging. To decrease this risk, regularly use a sunscreen with a broad spectrum SPF value of 15 or higher and other sun protection measures including: • limit time in the sun, especially from 10 a.m. – 2 p.m. • wear long sleeve shirts, pants, hats and sunglasses
- Reapply at least every 2 hours
- Use a water resistant sunscreen if swimming or sweating
- Children under 6 months: Ask a doctor

Inactive Ingredients

Ethyl Macadamiate, Caprylic/Capric Triglyceride, Saccharomyces Ferment, Coco Caprylate/Caprate, Behenyl Behenate, Sorbitol/Sebacic Acid Copolymer Behenate, Polyhydroxystearic Acid, Octyldodecyl Erucate, Euphorbia Cerifera (Candelilla) Wax, Fragrance/Parfum, Lauroyl Lysine, Iron Oxides, Stearic Acid, Alumina, Glyceryl Caprylate, Butyrospermum Parkii (Shea) Butter, Persea Gratissima (Avocado) Oil , Argania Spinosa Kernel Oil, Tocopheryl Acetate, Polyglyceryl-6 Polyricinoleate, Dilinoleic Acid/Butanediol Copolymer, Tocopherol, Glyceryl Undecylenate, Malic Acid, Castor Oil/IPDI Copolymer, Glycerin, Lycium Barbarum Fruit Extract , Punica Granatum Extract, Vitis Vinifera (Grape) Seed Extract, Aspalathus Linearis Leaf Extract , Leuconostoc/Radish Root Ferment Filtrate, Camellia Sinensis Leaf Extract, Limonene, Linalool, Citral.

Other information

■ Protect this product from excessive heat and direct sun

Questions or comments?

Call toll free 1-866-JUNEJACOBS ■ www.JUNEJACOBS.com